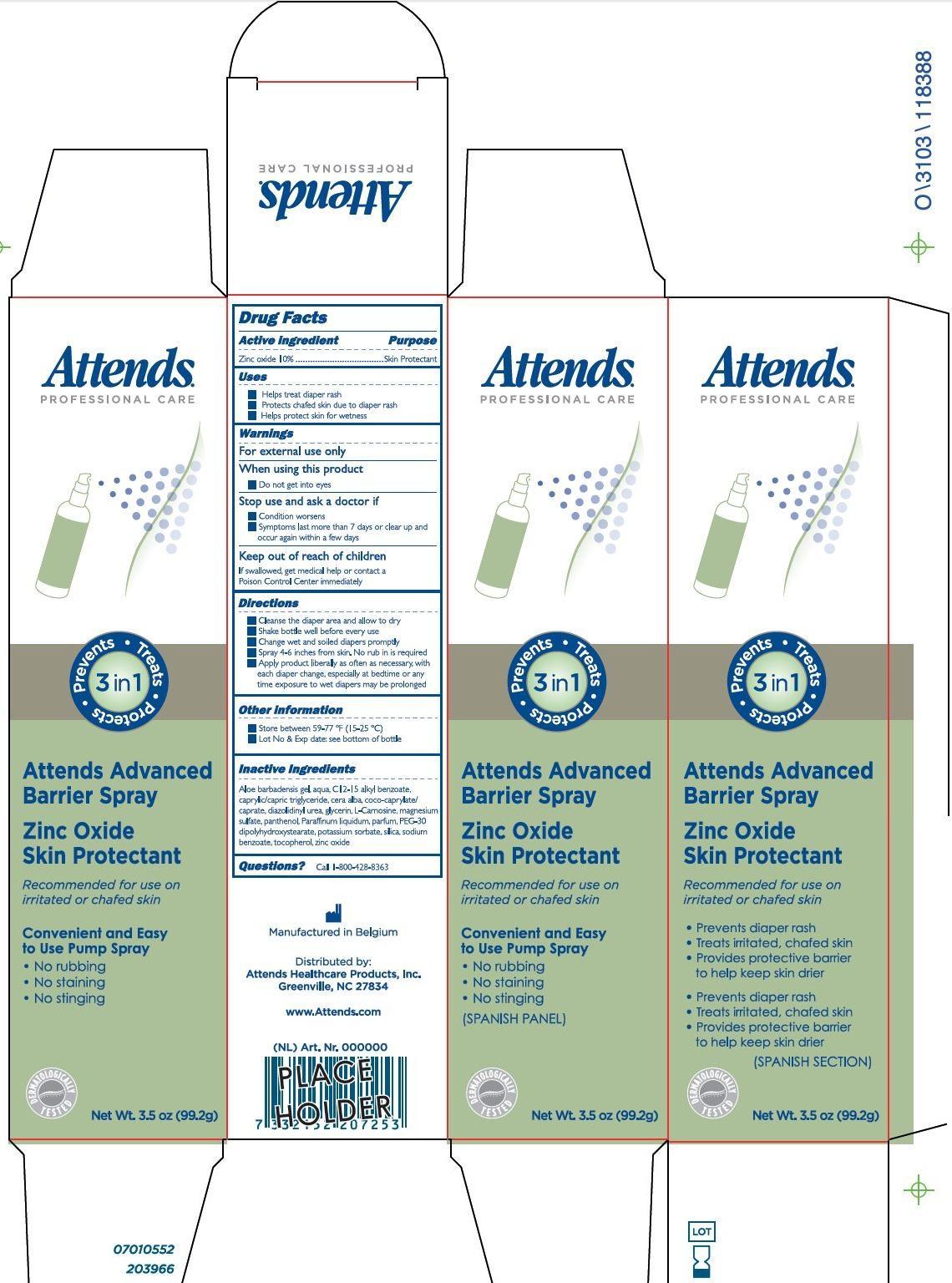 DRUG LABEL: Attends Advanced Barrier
NDC: 62450-002 | Form: SPRAY
Manufacturer: Purna Pharmaceuticals NV
Category: otc | Type: HUMAN OTC DRUG LABEL
Date: 20140306

ACTIVE INGREDIENTS: ZINC OXIDE 10 g/99 g
INACTIVE INGREDIENTS: ALOE VERA LEAF; WATER; C12-15 ALKYL BENZOATE; CAPRYLIC/CAPRIC/LAURIC TRIGLYCERIDE; WHITE WAX; COCO-CAPRYLATE/CAPRATE; DIAZOLIDINYL UREA; GLYCERIN; CARNOSINE; MAGNESIUM SULFATE; PANTHENOL; MINERAL OIL; PEG-30 DIPOLYHYDROXYSTEARATE; POTASSIUM SORBATE; SILICON DIOXIDE; SODIUM BENZOATE; TOCOPHEROL

Active Ingredient Purpose

Zinc Oxide 10% ................................. Skin Protectant

PURPOSE

Attends Professional Care

Prevents. Treats. Protects. 3in1

Attends Advanced Barrier S[ray

Zinc Oxide Skin Protectant

Recommended for use on irritated or chafed skin

Convenient and easy to use Pump Spray

- No rubbing
- No staining
- No stinging

(Spanish Panel)

- Prevents diaper rash
- Treats irritated, chafed skin
- Provides protective barrier to help keep skin drier

(Spanish Section

Dermatologically Tested

Net Wt. 3.5 oz (99.2 g)

Keep out of reach of children.

If swallowed, get medical help or contact a Poison Control Center immediately.

Uses

- Helps treat diaper rash
- Protects chafed skin due to diaper rash
- Helps protect skin for wetness

Warnings

For external use only

When using this product

- Do not get into eyes

Stop use and ask a doctor if

- Condition worsens
- Symptoms last more than 7 days or clear up and occur again within a few days

Directions

- Cleanse the diaper area and allow to dry
- Shake bottle well before every use
- Change wet and soiled diapers promptly
- Spray 4-6 inches from skin. No rub in is required
- Apply product liberally as often as necessary, with each dipaer change, especially at bedtime or any time exposure to wet diapers may be prolonged

Other Information

- Store between 59-77oF (15-25oC)
- Lot No & Exp date: see bottom of bottle

Questions? Call 1-800-428-8363

Manufactured in Belgium

Distributed by:

Attends Healthcare Products, Inc.

Greenville, NC 27834

www.Attends.com

Inactive Ingredients

aloe barbadensis gel, aqua, C12-15 alkyl benzoate, caprylic/capric triglyceride, cera alba, coco-caprylate/caprate, diazolidinyl urea, glycerin, L-Carnoside, magnesium sulfate, panthenol, paraffinum liquidum, parfum, PEG-30 dipolyhydroxystearate, potassium sorbate, silica, sodium benzoate, tocopherol, zinc oxide.